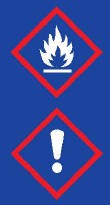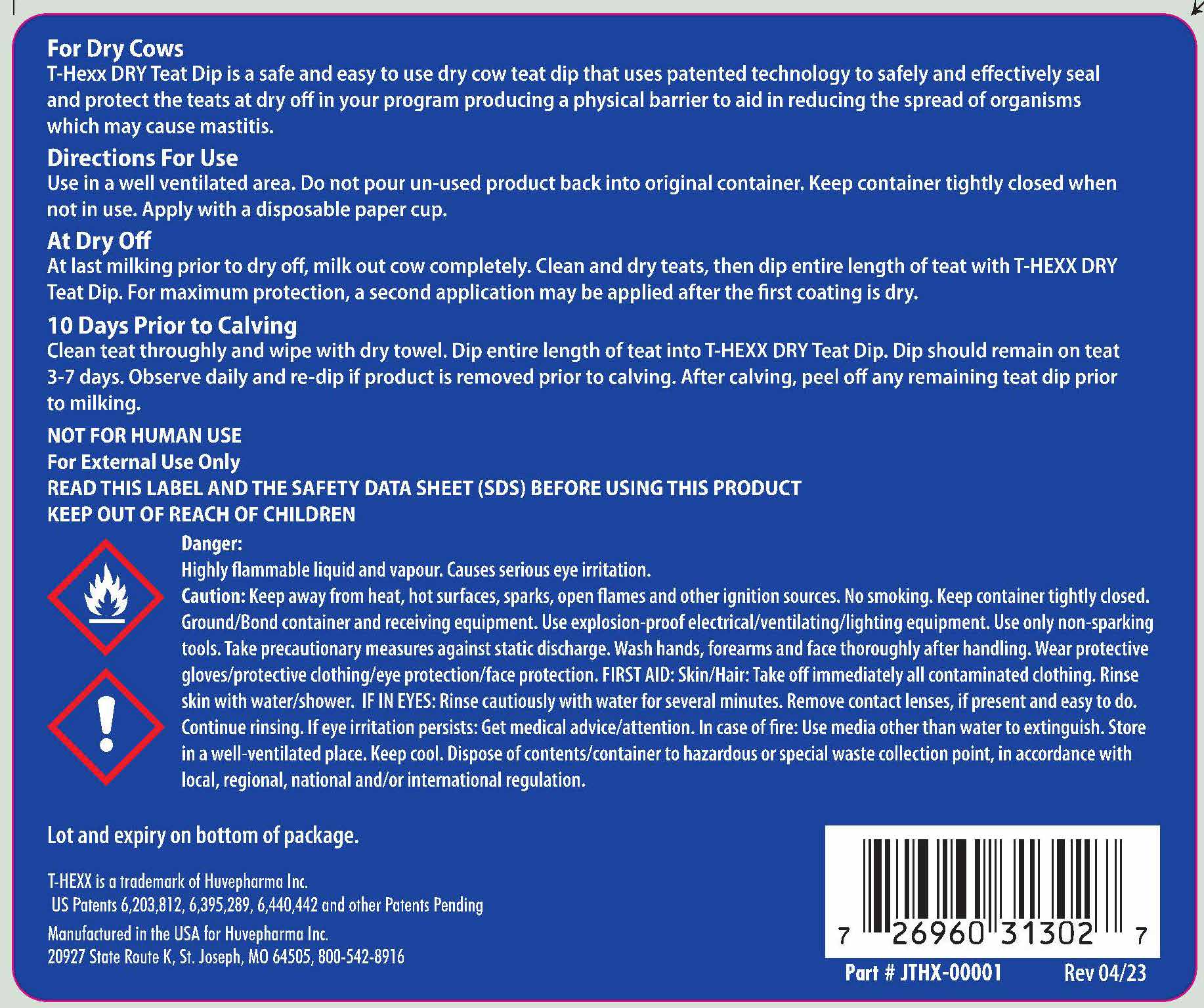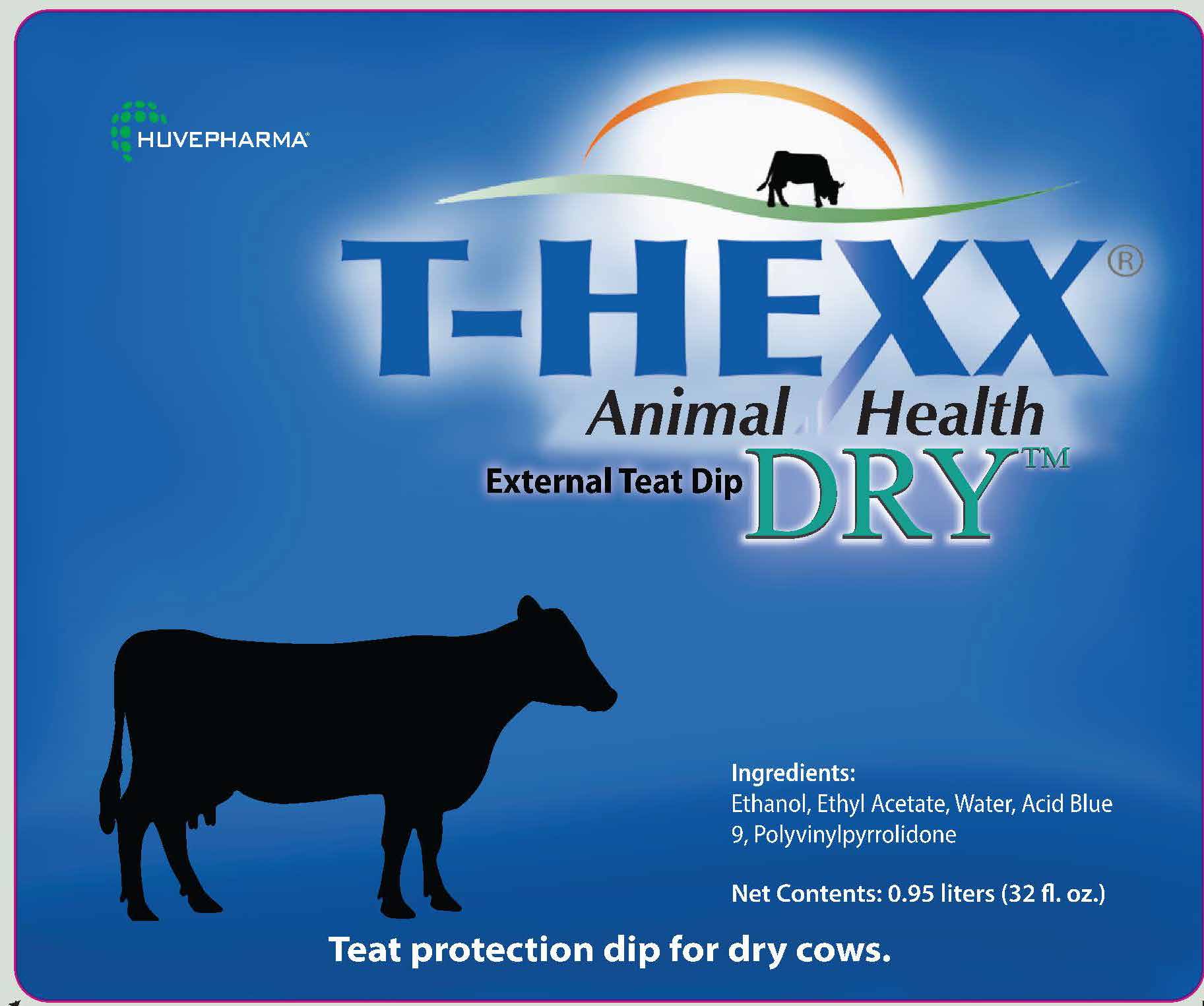 DRUG LABEL: T-HEXX Dry Teat Dip
NDC: 23243-8505 | Form: SOLUTION
Manufacturer: Huvepharma, Inc
Category: animal | Type: OTC ANIMAL DRUG LABEL
Date: 20230919

ACTIVE INGREDIENTS: POVIDONE .910 g/1 L
INACTIVE INGREDIENTS: ALCOHOL; Water; ETHYL ACETATE; ACID BLUE 9 AMMONIUM

T-HEXX Dry Teat Sealant

T-HEXX®
Animal Health
External Teat Dip DRY™

INACTIVE INGREDIENT

Ingredients:

Ethanol, Ethyl Acetate, Water, Acid Blue 9, Polyvinylpyrrolidone

Net Contents: 0.95 liters (32 fl. oz.)

Teat protection dip for dry cows.

INDICATIONS AND USAGE

For Dry Cows
T-Hexx DRY Teat Dip is a safe and easy to use dry cow teat dip that uses patented technology to safely and effectively seal
and protect the teats at dry off in your program producing a physical barrier to aid in reducing the spread of organisms
which may cause mastitis.

Directions For Use
Use in a well ventilated area. Do not pour ununused product back into original container. Keep container tightly closed when
not in use. Apply with a disposable paper cup.

At Dry Off
At last milking prior to dry off, milk out cow completely. Clean and dry teats, then dip entire length of teat with T-HEXX DRY
Teat Dip. For maximum protection, a second application may be applied after the first coating is dry.

10 Days Prior to Calving
Clean teat throughly and wipe with dry towel. Dip entire length of teat into T-HEXX DRY Teat Dip. Dip should remain on teat
3-7 days. Observe daily and re-dip if product is removed prior to calving. After calving, peel off any remaining teat dip prior
to milking.

USER SAFETY WARNINGS

NOT FOR HUMAN USE
For External Use Only
READ THIS LABEL AND THE SAFETY DATA SHEET (SDS) BEFORE USING THIS PRODUCT
KEEP OUT OF REACH OF CHILDREN

Danger:
Highly flammable liquid and vapour. Causes serious eye irritation.
Caution: Keep away from heat, hot surfaces, sparks, open flames and other ignition sources. No smoking. Keep container tightly closed.
Ground/Bond container and receiving equipment. Use explosion-proof electrical/ventilating/lighting equipment. Use only non-sparking
tools. Take precautionary measures against static discharge. Wash hands, forearms and face thoroughly after handling. Wear protective
gloves/protective clothing/eye protection/face protection. FIRST AID: Skin/Hair: Take off immediately all contaminated clothing. Rinse
skin with water/shower. IF IN EYES: Rinse cautiously with water for several minutes. Remove contact lenses, if present and easy to do.
Continue rinsing. If eye irritation persists: Get medical advice/attention. In case of fire: Use media other than water to extinguish. Store
in a well-ventilated place. Keep cool. Dispose of contents/container to hazardous or special waste collection point, in accordance with
local, regional, national and/or international regulation.

Lot and expiry on bottom of package.

T-HEXX is a trademark of Huvepharma Inc.

US Patents 6,203,812, 6,395,289, 6,440,442 and other Patents Pending

Manufactured in the USA for Huvepharma Inc.

20927 State Route K, St. Joseph, MO 64505, 800-542-8916